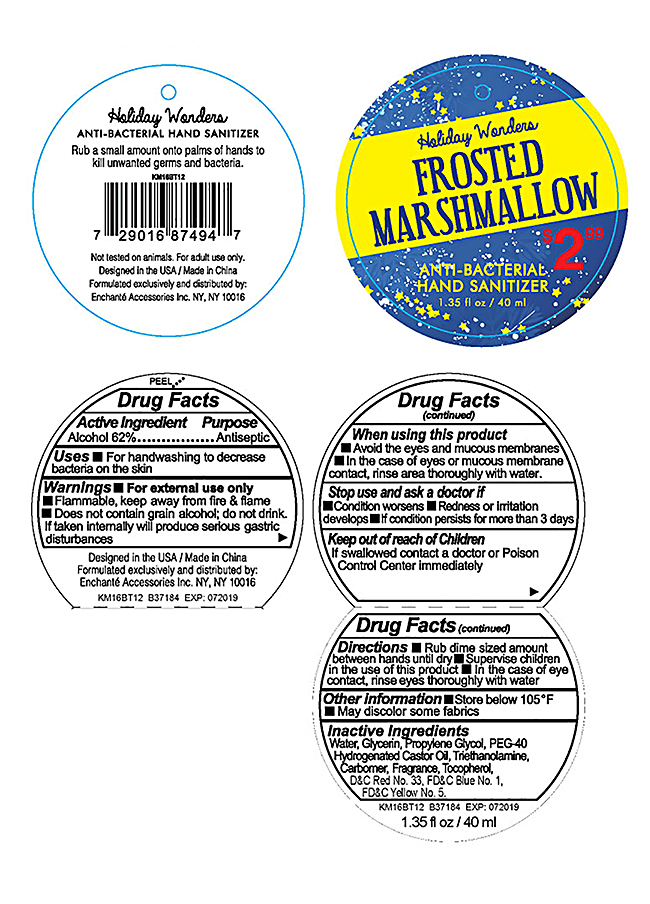 DRUG LABEL: Holiday Wonders Frosted Marshmallow Antibacterial Hand Sanitizer
NDC: 50563-191 | Form: LIQUID
Manufacturer: ENCHANTE ACCESSORIES INC.
Category: otc | Type: HUMAN OTC DRUG LABEL
Date: 20160816

ACTIVE INGREDIENTS: ALCOHOL 62 mL/100 mL
INACTIVE INGREDIENTS: WATER; CARBOMER COPOLYMER TYPE A; TROLAMINE; GLYCERIN; D&C RED NO. 33; FD&C BLUE NO. 1; FD&C YELLOW NO. 5; PROPYLENE GLYCOL; PEG-40 CASTOR OIL; TOCOPHEROL

Drug Fact

Active Ingredient

Ethyl Alcohol 62%

Purpose

Antiseptic

Uses

For hand washing to decrease bacteria on the skin

WARNINGS

For external use only-hands

Flammable. Keep away from heat and flame

Does not contain grain alcohol, do not drink. If taken internally will produce serious gastric disturbances

When using this product

Avoid the eyes and mucous membranes

In case of eye or mucous membrane contact, rinse area thoroughly with water

Stop use and ask a doctor if

Condiiton worsens

Redness or irritation develops

If condition persists for more than three days

Keep out of reach of children.

If swallowed, contact a doctor or a Poison Control Center immediately.

Directions

- Rub dime sized amount between hands until dry
- Supervise children in the use of this product
- In the case of eye contact, rinse eyes thoroughly with water

Other Information

Store below 105F

May discolor some fabrics

Inactive Ingredient:

Water, Glycerin, Propylene Glycol, FEG-40 Hydrogenated Castor Oil, Triethanolamine, Carbomer, tocopherol, Fragrance, D and C Red No. 33, FD and C Blue No. 1, FD and C Yellow No. 5,